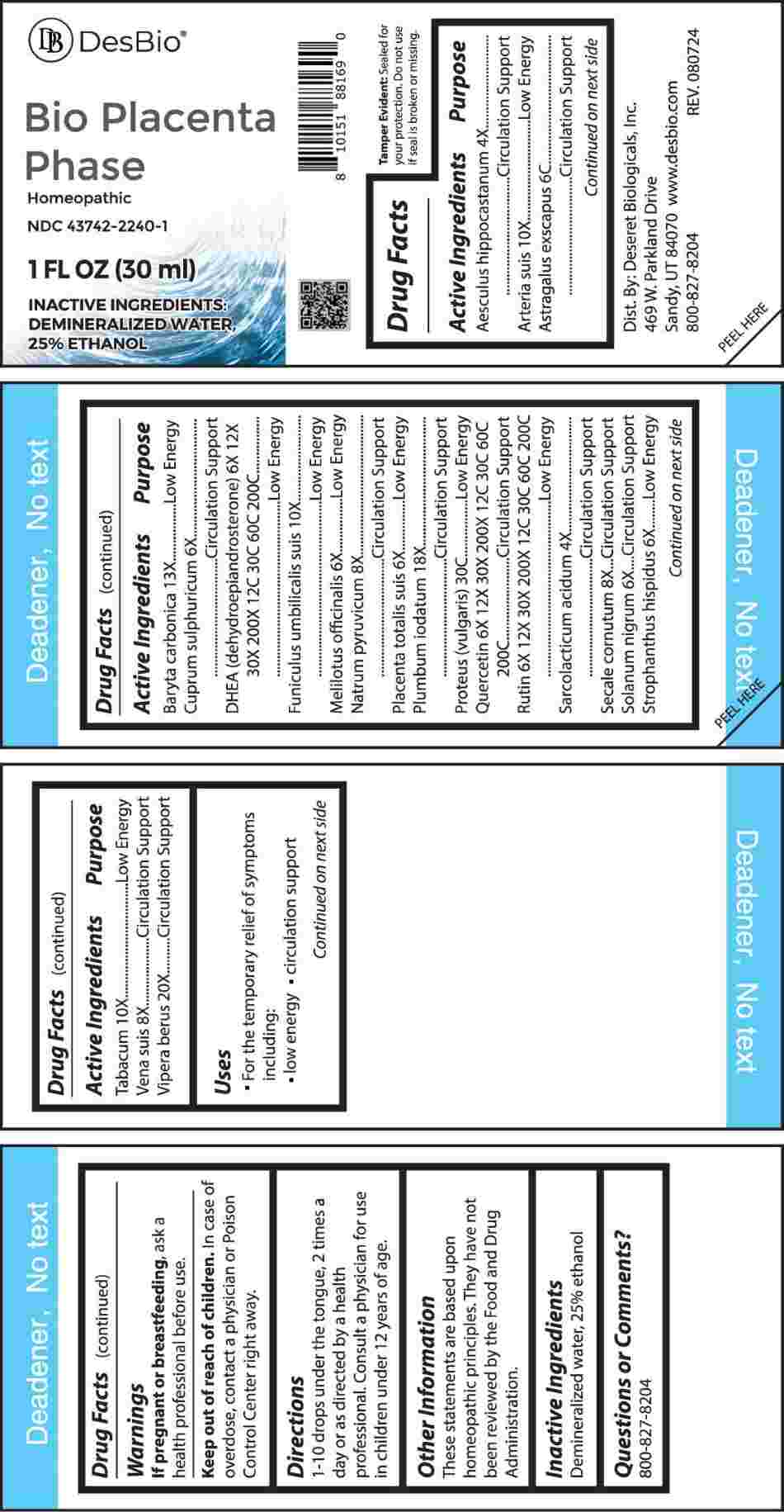 DRUG LABEL: Bio Placenta Phase
NDC: 43742-2240 | Form: LIQUID
Manufacturer: Deseret Biologicals, Inc.
Category: homeopathic | Type: HUMAN OTC DRUG LABEL
Date: 20241118

ACTIVE INGREDIENTS: HORSE CHESTNUT 4 [hp_X]/1 mL; SUS SCROFA ARTERY 10 [hp_X]/1 mL; ASTRAGALUS EXSCAPUS WHOLE FLOWERING/FRUITING 6 [hp_C]/1 mL; BARIUM CARBONATE 13 [hp_X]/1 mL; CUPRIC SULFATE 6 [hp_X]/1 mL; PRASTERONE 6 [hp_X]/1 mL; SUS SCROFA UMBILICAL CORD 10 [hp_X]/1 mL; MELILOTUS OFFICINALIS TOP 6 [hp_X]/1 mL; SODIUM PYRUVATE 8 [hp_X]/1 mL; SUS SCROFA PLACENTA 6 [hp_X]/1 mL; LEAD IODIDE 18 [hp_X]/1 mL; PROTEUS VULGARIS 30 [hp_C]/1 mL; QUERCETIN 6 [hp_X]/1 mL; RUTIN 6 [hp_X]/1 mL; LACTIC ACID, L- 4 [hp_X]/1 mL; CLAVICEPS PURPUREA SCLEROTIUM 8 [hp_X]/1 mL; SOLANUM NIGRUM WHOLE 6 [hp_X]/1 mL; STROPHANTHUS HISPIDUS SEED 6 [hp_X]/1 mL; TOBACCO LEAF 10 [hp_X]/1 mL; SUS SCROFA VEIN 8 [hp_X]/1 mL; VIPERA BERUS VENOM 20 [hp_X]/1 mL
INACTIVE INGREDIENTS: water; ALCOHOL

DRUG FACTS:

ACTIVE INGREDIENTS:

Aesculus Hippocastanum 4X, Arteria Suis 10X, Astragalus Exscapus 6C, Baryta Carbonica 13X, Cuprum Sulphuricum 6X, DHEA (Dehydroepiandrosterone) 6X, 12X, 30X, 200X, 12C, 30C, 60C, 200C, Funiculus Umbilicalis Suis 10X, Melilotus Officinalis 6X, Natrum Pyruvicum 8X, Placenta Totalis Suis 6X, Plumbum Iodatum 18X, Proteus (Vulgaris) 30C, Quercetin 6X, 12X, 30X, 200X, 12C, 30C, 60C, 200C, Rutin 6X, 12X, 30X, 200X, 12C, 30C, 60C, 200C, Sarcolacticum Acidum 4X, Secale Cornutum 8X, Solanum Nigrum 6X, Strophanthus Hispidus 6X, Tabacum 10X, Vena Suis 8X, Vipera Berus 20X.

PURPOSE:

Aesculus Hippocastanum – Circulation Support, Arteria Suis – Low Energy, Astragalus Exscapus – Circulation Support, Baryta Carbonica – Low Energy, Cuprum Sulphuricum – Circulation Support, DHEA (Dehydroepiandrosterone) – Low Energy, Funiculus Umbilicalis Suis – Low Energy, Melilotus Officinalis – Low Energy, Natrum Pyruvicum – Circulation Support, Placenta Totalis Suis – Low Energy, Plumbum Iodatum – Circulation Support, Proteus (Vulgaris) – Low Energy, Quercetin – Circulation Support, Rutin – Low Energy, Sarcolacticum Acidum – Circulation Support, Secale Cornutum – Circulation Support, Solanum Nigrum – Circulation Support, Strophanthus Hispidus – Low Energy, Tabacum – Low Energy, Vena Suis - Circulation Support, Vipera Berus – Circulation Support

USES:

• For the temporary relief of symptoms including:

• low energy • circulation support

These statements are based upon homeopathic principles. They have not been reviewed by the Food and Drug Administration.

WARNINGS:

If pregnant or breast-feeding, ask a health professional before use.

Keep out of reach of children. In case of overdose, contact a physician or Poison Control Center right away.

Tamper Evident: Sealed for your protection. Do not use if seal is broken or missing.

KEEP OUT OF REACH OF CHILDREN:

In case of overdose, contact a physician or Poison Control Center right away.

DIRECTIONS:

1-10 drops under the tongue, 2 times a day or as directed by a health professional. Consult a physician for use in children under 12 years of age.

INACTIVE INGREDIENTS:

Demineralized water, 25% ethanol

QUESTIONS:

Dist. By: Deseret Biologicals, Inc.

469 W. Parkland Drive

Sandy, UT 84070

www.desbio.com

800-827-8204

PACKAGE LABEL DISPLAY:

DesBio

Bio Placenta

Phase

Homeopathic

NDC 43742-2240-1

1 FL OZ (30 ml)